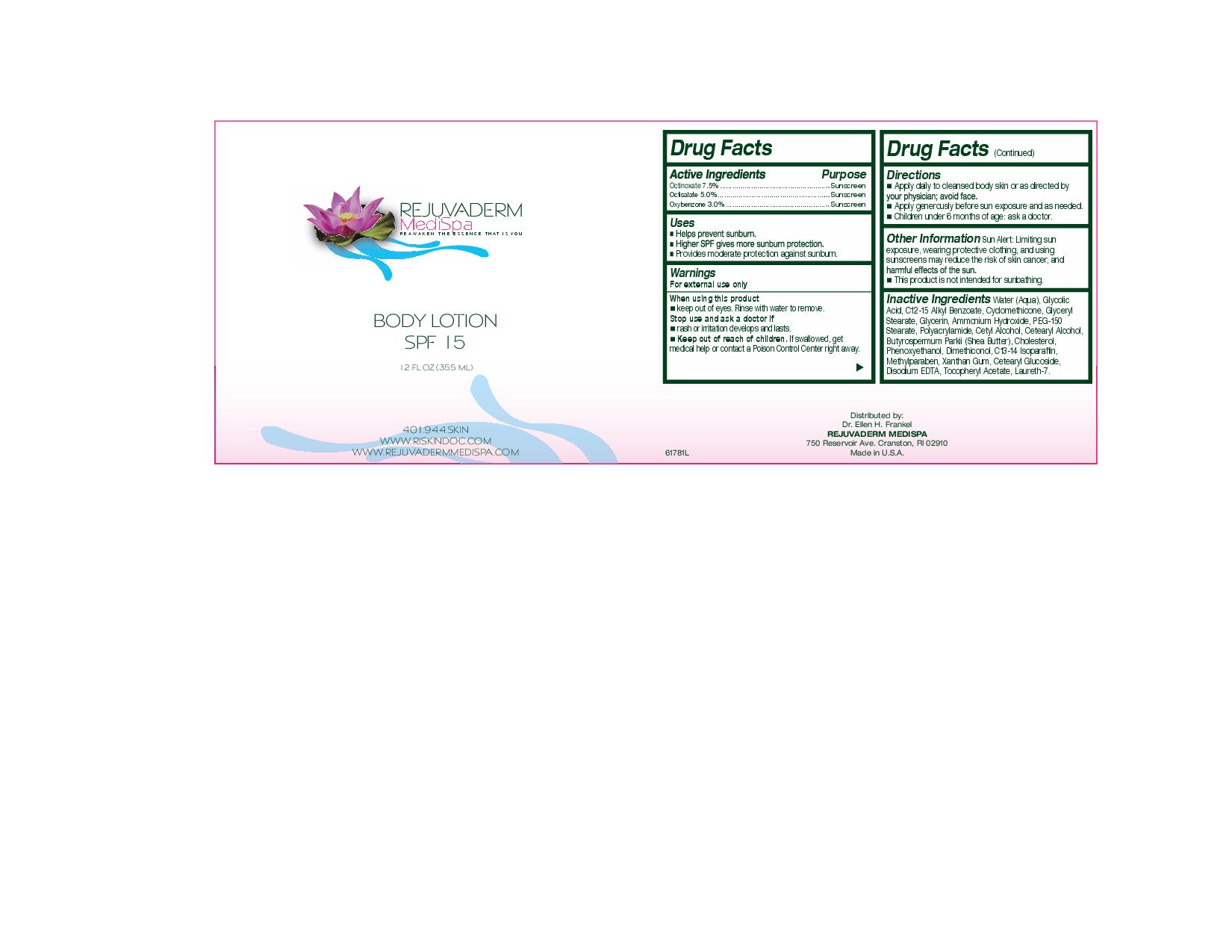 DRUG LABEL: Rejuvaderm Medispa Body
NDC: 51325-200 | Form: LOTION
Manufacturer: Ellen H Frankle MD Inc
Category: otc | Type: HUMAN OTC DRUG LABEL
Date: 20100803

ACTIVE INGREDIENTS: Octinoxate 26.625 mL/355 mL; Octisalate 17.75 mL/355 mL; Oxybenzone 10.65 mL/355 mL

Rejuvaderm Medispa Body

Active Ingredients Purpose

Octinoxate 7.5% Sunscreen

Octisalate 5.0% Sunscreen

Oxybenzone 3.0% Sunscreen

Uses

Helps prevent sunburn.

Higher SPF gives more sunburn protection.

Provides moderate protection against sunburn.

Warnings

For external use only

When using this product

- keep out of eyes. Rinse with water to remove.

Stop use and ask a doctor if

- rash or irritation develops and lasts.

- Keep out of reach of children. If swallowed, get medical help or contact a Poison Control Center right away.

INACTIVE INGREDIENT

Inactive Ingredients Water (Aqua), Glycolic Acid, C12-15 Alkyl Benzoate, Cyclomethicone, Glyceryl Stearate, Glycerin, Ammonium Hydroxide, PEG-150 Stearate, Polyacrylamide, Cetyl alcohol, Cetearyl Alcohol, Butyrospermum Parkii (shea butter), Cholesterol, Phenozyethanol,Dimethiconol, C13-14 Isoparaffin, Methylparaben, Xanathan gum, cetearyl glucoside, Disodium EDTA, Tocopheryl acetate, Laureth-7

Directions:

- Apply daily to cleansed body skin or as directed by your physician; avoid face.
- Apply generously before sun exposure and as needed.
- Children under 6 months of age: ask a doctor.

Other Information
Sun alert: Limiting sun exposure, wearing protective clothing, and using sunscreens may reduce the risk of skin cancer, and harmful effects of the sun.
This product is not intended for sunbathing.

PACKAGE LABEL

Rejuvaderm Medispa
Reawaken the essence that is you
Body Lotion
SPF 15
12 fl oz (355 ml)
401944skin
www.riskindoc.com
www.rejuvadermmedispa.com